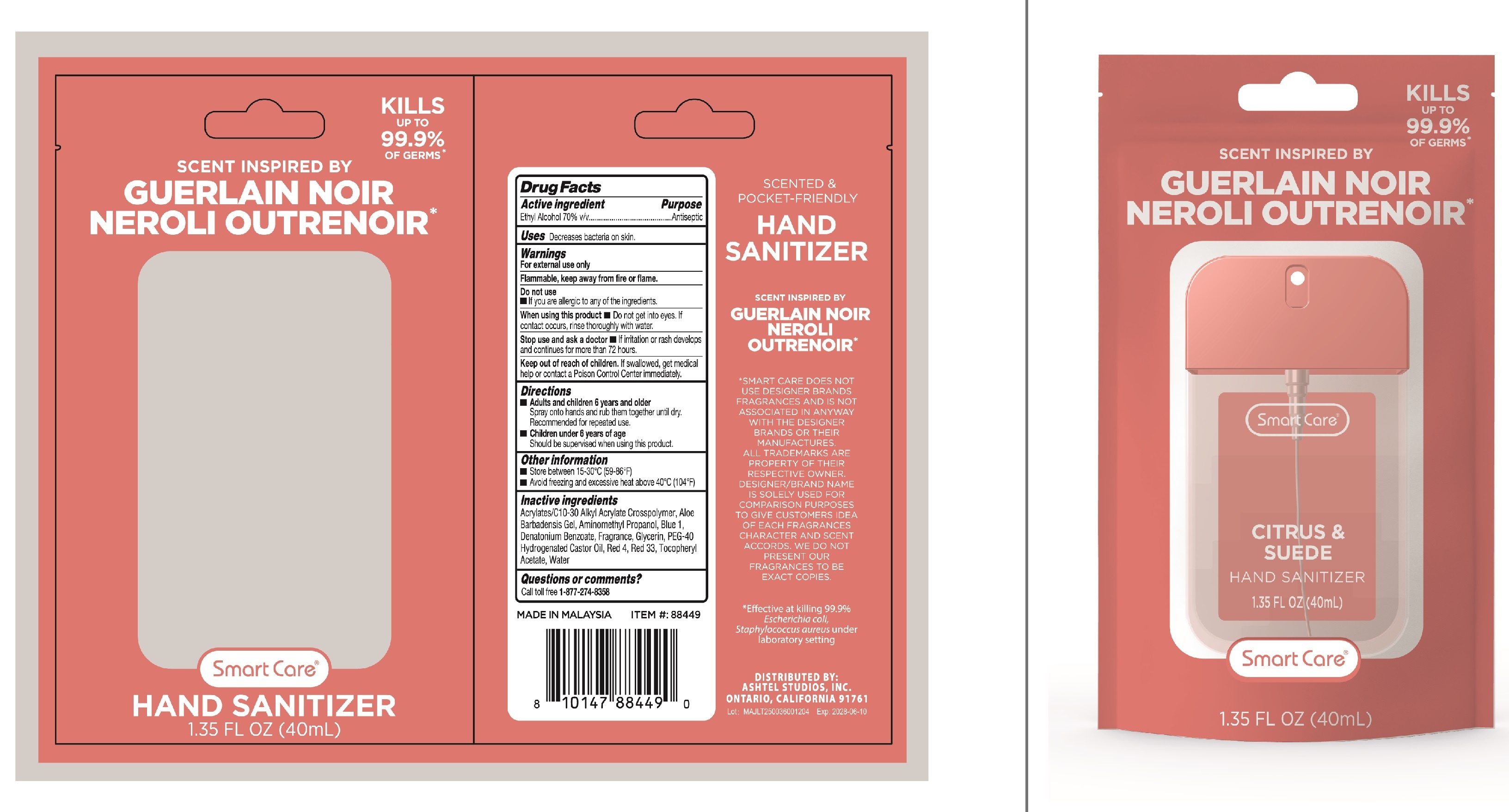 DRUG LABEL: Smart Care Luxury Hand Sanitizer  Citrus Suede
NDC: 87016-006 | Form: SPRAY
Manufacturer: LANTERN HEALTH & BEAUTY SDN. BHD.
Category: otc | Type: HUMAN OTC DRUG LABEL
Date: 20250815

ACTIVE INGREDIENTS: ALCOHOL 70 mL/100 mL
INACTIVE INGREDIENTS: D&C RED NO. 33; FD&C BLUE NO. 1; FD&C RED NO. 4; AMINOMETHYL PROPANOL; POLYOXYL 40 HYDROGENATED CASTOR OIL; .ALPHA.-TOCOPHEROL ACETATE; GLYCERIN; WATER; ACRYLATES/C10-30 ALKYL ACRYLATE CROSSPOLYMER (60000 MPA.S); DENATONIUM BENZOATE; ALOE VERA LEAF

Smart Care Luxury Hand Sanitizer Citrus Suede

Active Ingredient

Active ingredient ... Purpose
Ethyl Alcohol 70% v/v...Antiseptic

Uses

Decreases bacteria on skin.

Warning

For external use only
Flammable, keep away from fire or flame.

when using this product

Do not get into eyes. If contact occurs, rinse thoroughly with water.

Do not use

If you are allergic to any of the ingredients.

stop use and ask a doctor

If irritation or rash develops and continues for more than 72 hours.

keep out of reach of children

If swallowed get medical help or contact a Poison Control Center immediately.

Directions

Adults and children 6 years and older
Spray onto hands and rub them together until dry.
Recommended for repeated use.
Children under 6 year of age
Should be supervised when using this product.

Inactive ingredients

Acrylates/C10-30 Alkyl Acrylate Crosspolymer, Aloe Barbadensis Gel, Aminomethyl Propanol, Blue 1, Denatonium Benzoate, Fragrance, Glycerin, Peg-40 Hydrogenated Castor Oil, Red 4, Red 33,Tocopheryl Acetate, Watre.

other Information

Store between 15-30°C(59-86°F)
Avoid freezing and excessive heat above 40°℃ (104°F)

Questions or comments?

Call toll free 1-877-274-8358

packing